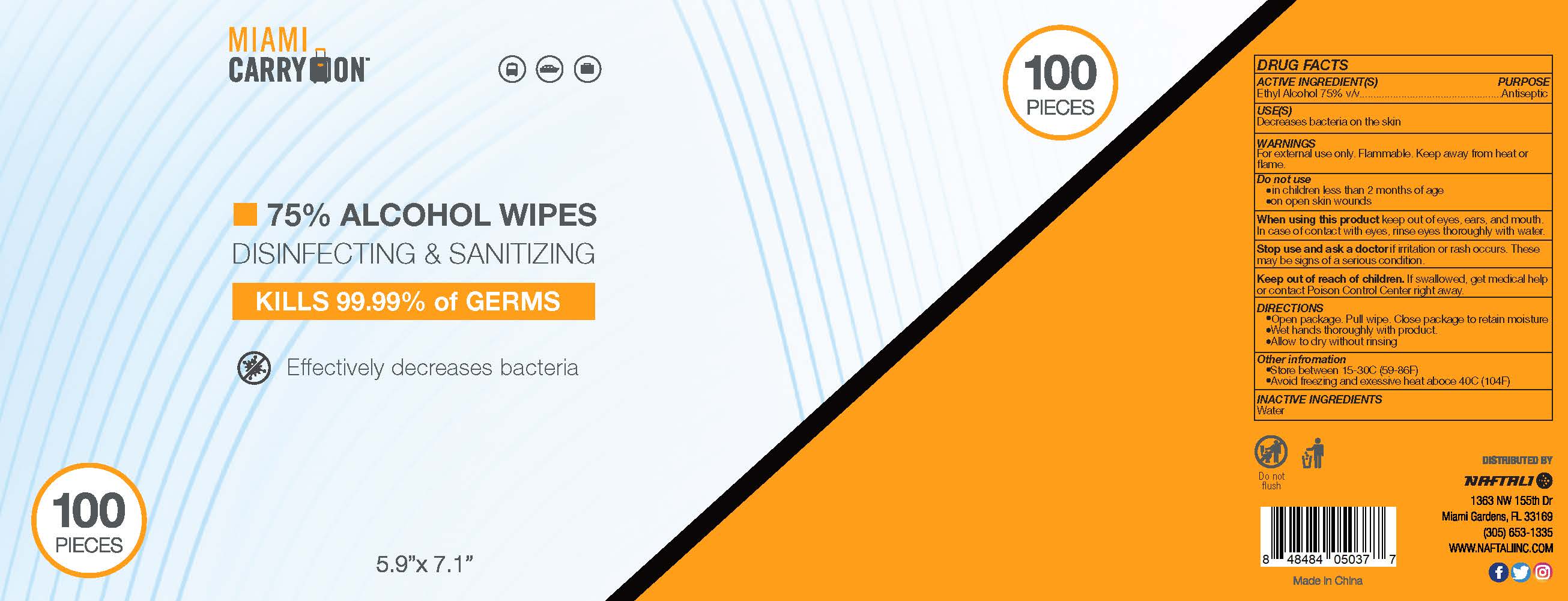 DRUG LABEL: Alcohol Wipes
NDC: 80213-101 | Form: CLOTH
Manufacturer: Zhejiang Chenwei Daily Chemicals Technology Co.,Ltd.
Category: otc | Type: HUMAN OTC DRUG LABEL
Date: 20200823

ACTIVE INGREDIENTS: ALCOHOL 3.75 mL/1 1
INACTIVE INGREDIENTS: WATER

Chenwei Wipes Alcohol 75%, 100ct

ACTIVE INGREDIENT(S)

Ethyl Alcohol: 75% v/v ...... Purpose: Antiseptic

PURPOSE

Antiseptic

WARNINGS

For external use only. Flammable. Keep away from heat or flame.

Do not use

- in children less than 2 months of age
- on open skin wounds

Stop use and ask a doctor

if irritation or rash occurs. These may be signs of a serious condition.

Keep out of reach of children.

If swallowed, get medical help or contact Poison Control Center right away.

USE(S)

Decreases bacteria on the skin.

DIRECTIONS

- Open the package. Pull wipe. Close package to retain mositure
- Wet hands thoroghly with product
- Allow to dry without rinsing

When using this product

keep out of eyes, ears, and mouth. In case of contact with eyes, rinse eyes thoroughly with water.

Other information

- Store between 15-30℃ (59-86℉)
- Avoid freezing and excessive heat above 40℃ (104℉)

INACTIVE INGREDIENTS

Water